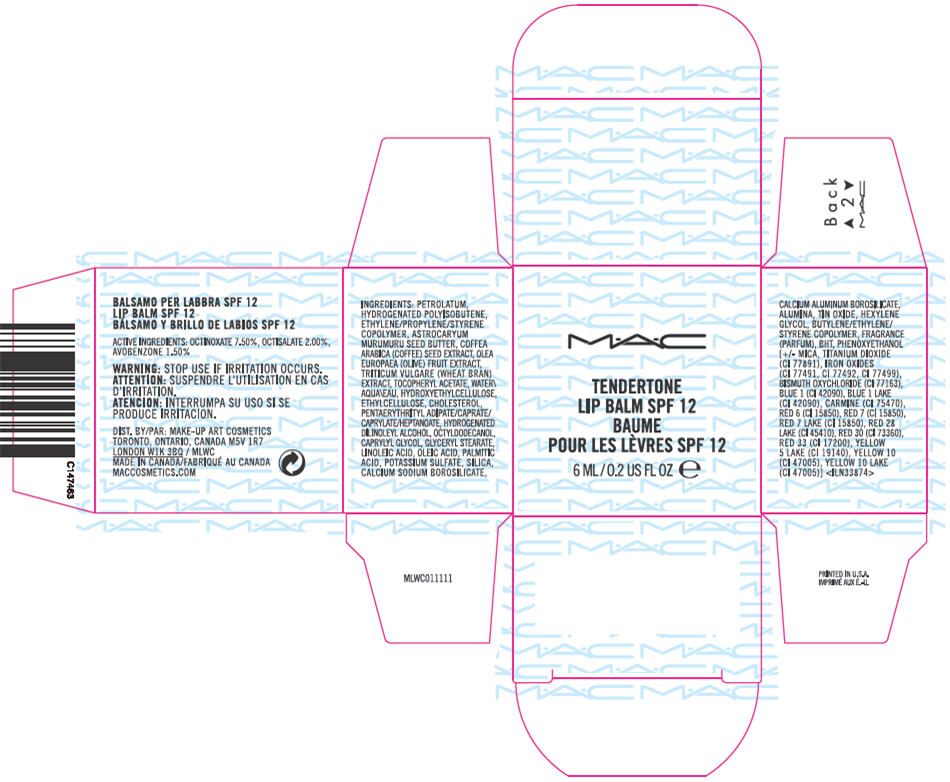 DRUG LABEL: TENDERTONE LIP BALM SPF 12
NDC: 40046-0030 | Form: LIPSTICK
Manufacturer: MAKEUP ART COSMETICS
Category: otc | Type: HUMAN OTC DRUG LABEL
Date: 20120117

ACTIVE INGREDIENTS: OCTINOXATE 7.5 mL/100 mL; OCTISALATE 2 mL/100 mL; AVOBENZONE 1.5 mL/100 mL
INACTIVE INGREDIENTS: Petrolatum; Astrocaryum Murumuru Seed Butter; Arabica Coffee Bean; Black Olive; Wheat Bran; Alpha-Tocopherol Acetate; Water; Ethylcelluloses; Cholesterol; Octyldodecanol; Caprylyl Glycol; Glyceryl Monostearate; Linoleic Acid; Oleic Acid; Palmitic Acid; Potassium Sulfate; Silicon Dioxide; Aluminum Oxide; Stannic Oxide; Hexylene Glycol; Butylated Hydroxytoluene; Phenoxyethanol; Mica; Titanium Dioxide; Ferric Oxide Red; Ferric Oxide Yellow; Ferrosoferric Oxide; Bismuth Oxychloride; FD&C Blue No. 1; Cochineal; D&C Red No. 6; D&C Red No. 7; D&C Red No. 28; D&C Red No. 30; D&C Red No. 33; FD&C Yellow No. 5; D&C Yellow No. 10

MAC
TENDERTONE
LIP BALM SPF 12

ACTIVE INGREDIENTS

OCTINOXATE 7.50%, OCTISALATE 2.00%, AVOBENZONE 1.50%

WARNING

STOP USE IF IRRITATION OCCURS.

INGREDIENTS

PETROLATUM, HYDROGENATED POLYISOBUTENE, ETHYLENE/PROPYLENE/STYRENE COPOLYMER, ASTROCARYUM MURUMURU SEED BUTTER, COFFEA ARABICA (COFFEE) SEED EXTRACT, OLEA EUROPAEA (OLIVE) FRUIT EXTRACT, TRITICUM VULGARE (WHEAT BRAN) EXTRACT, TOCOPHERYL ACETATE, WATER, HYDROXYETHYLCELLULOSE, ETHYLCELLULOSE, CHOLESTEROL, PENTAERYTHRITYL ADIPATE/CAPRATE/CAPRYLATE/HEPTANOATE, HYDROGENATED DILINOLEYL ALCOHOL, OCTYLDODECANOL, CAPRYLYL GLYCOL, GLYCERYL STEARATE, LINOLEIC ACID, OLEIC ACID, PALMITIC ACID, POTASSIUM SULFATE, SILICA, CALCIUM SODIUM BOROSILICATE, CALCIUM ALUMINUM BOROSILICATE, ALUMINA, TIN OXIDE, HEXYLENE GLYCOL, BUTYLENE/ETHYLENE/STYRENE COPOLYMER, FRAGRANCE, BHT, PHENOXYETHANOL [+/- MICA, TITANIUM DIOXIDE (CI 77891), IRON OXIDES (CI 77491, CI 77492, CI 77499), BISMUTH OXYCHLORIDE (CI 77163), BLUE 1 (CI 42090), BLUE 1 LAKE (CI 42090), CARMINE (CI 75470), RED 6 (CI 15850), RED 7 (CI 15850), RED 7 LAKE (CI 15850), RED 28 LAKE (CI 45410), RED 30 (CI 73360), RED 33 (CI 17200), YELLOW 5 LAKE (CI 19140), YELLOW 10 (CI 47005), YELLOW 10 LAKE (CI 47005)] <ILN33874>

DIST. BY: MAKE-UP ART COSMETICS
TORONTO, ONTARIO, CANADA M5V 1R7
LONDON W1K 3BQ / MLWC

PRINCIPAL DISPLAY PANEL - 6 ML Jar Carton

MAC

TENDERTONE
LIP BALM SPF 12

6 ML/0.2 US FL OZ e